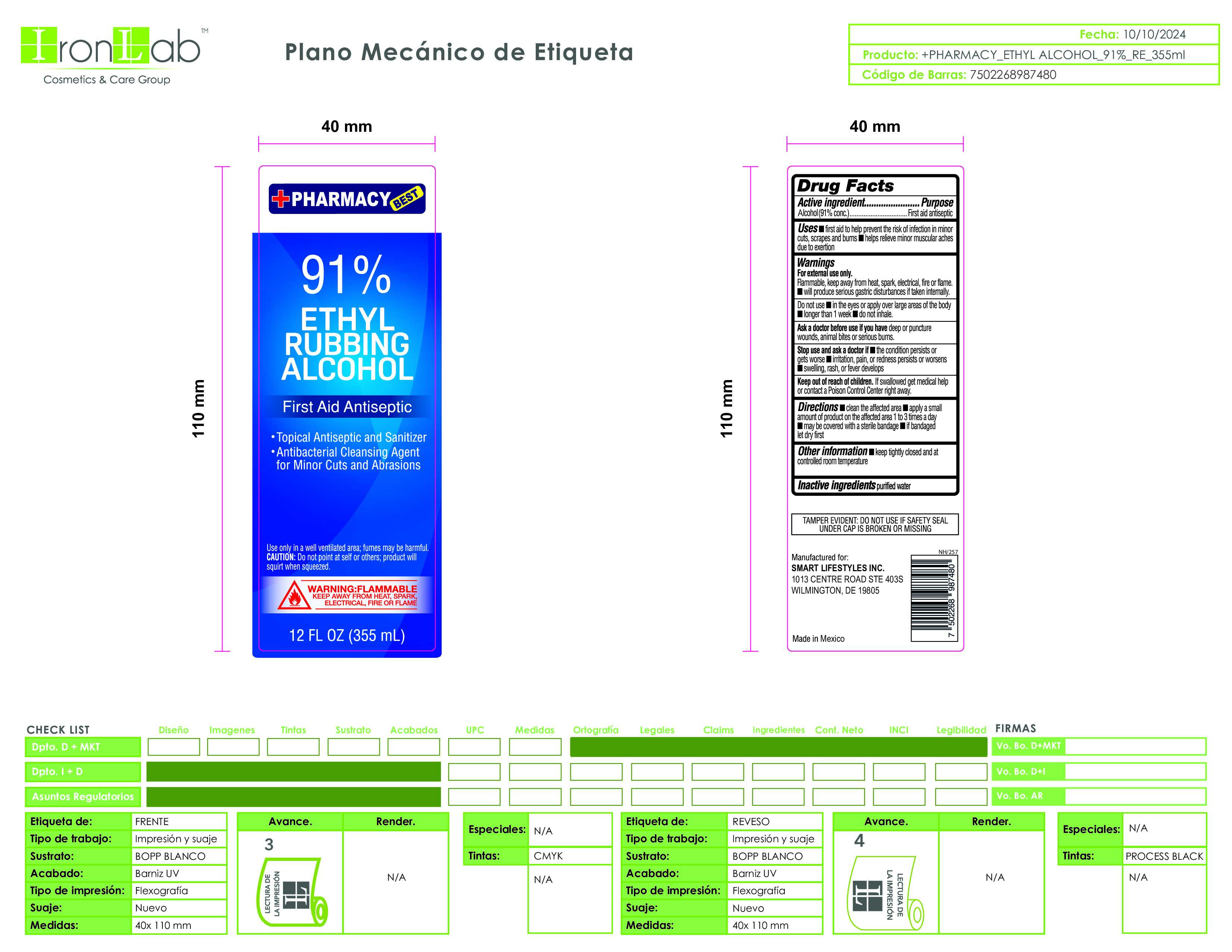 DRUG LABEL: Ethyl Rubbing Alcohol
NDC: 74375-020 | Form: LIQUID
Manufacturer: Iron Lab SA de CV
Category: otc | Type: HUMAN OTC DRUG LABEL
Date: 20260217

ACTIVE INGREDIENTS: ALCOHOL 91 mL/100 mL
INACTIVE INGREDIENTS: WATER

91 Rubbing Alcohol Iron Lab SA de CV

ACTIVE INGREDIENT

91% Ethyl Alcohol

DOSAGE AND ADMINISTRATION

Thoroughly cover your hands with product and allow to dry without wiping. Children under 6 years of age should be supervised when using this product. Not recommended for infants.

INSTRUCTIONS FOR USE

Thoroughly cover your hands with product and allow to dry without wiping. Children under 6 years of age should be supervised when using this product. Not recommended for infants.

INACTIVE INGREDIENT

Purified Water

STOP USE

Irritation or redness develops. Condition persist for more than 72 hours.

PURPOSE

To decrease bacteria on the skin that could cause disease. Recommended for repeated use.

WARNINGS

For external use only: hands. Flammable, Keep away from fire of flame.

KEEP OUT OF REACH OF CHILDREN

If swallowed, get medical help or contact a Poison Control Center right away

ASK DOCTOR

Irritation or redness develops. Condition persist for more than 72 hours.

OTHER SAFETY INFORMATION

Store below 105°F. May discolor some fabrics. Harmful to wood finishes and plastic

INDICATIONS AND USAGE

Thoroughly cover your hands with product and allow to dry without wiping. Children under 6 years of age should be supervised when using this product. Not recommended for infants.

PACKAGE LABEL

Ethyl Rubbing Alcohol 91